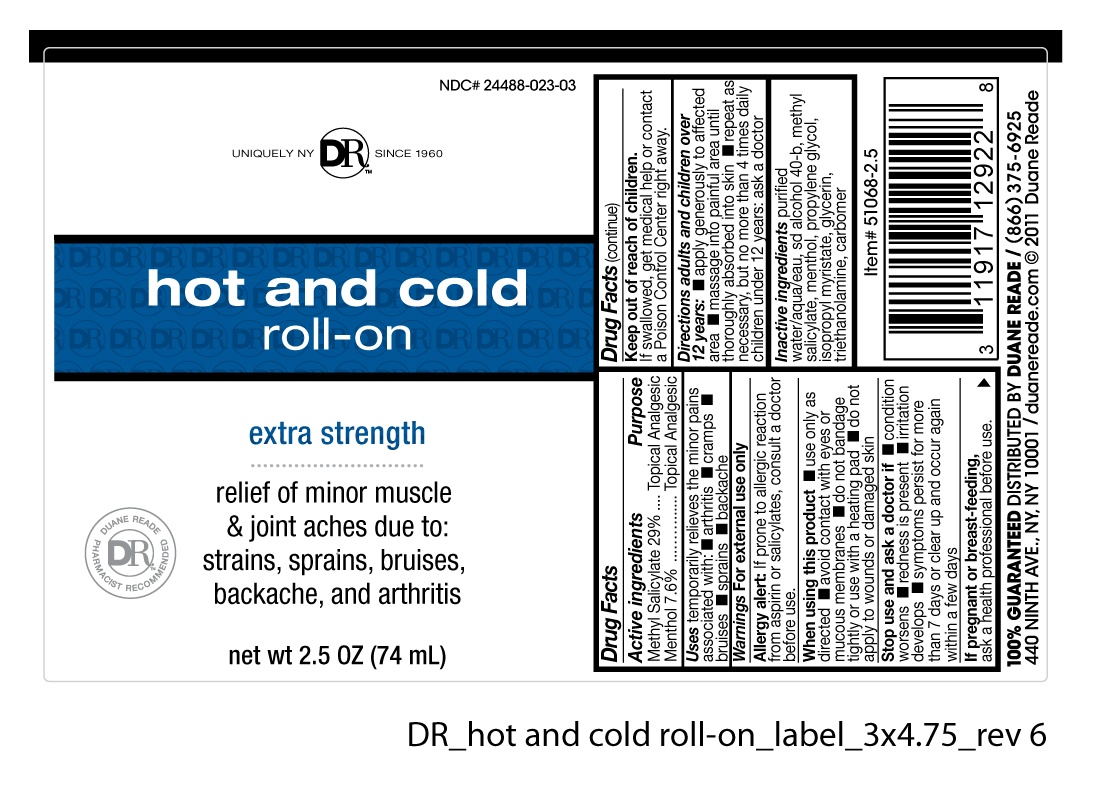 DRUG LABEL: Duane Reade
NDC: 24488-023 | Form: GEL
Manufacturer: Duane Reade
Category: otc | Type: HUMAN OTC DRUG LABEL
Date: 20110225

ACTIVE INGREDIENTS: METHYL SALICYLATE 21.46 mL/74 mL; MENTHOL 5.62 mL/74 mL
INACTIVE INGREDIENTS: WATER ; ALCOHOL; PROPYLENE GLYCOL ; ISOPROPYL MYRISTATE; GLYCERIN; TROLAMINE; CARBOMER INTERPOLYMER TYPE A (55000 MPA.S)

Drug Facts

Active Ingredients Purpose

Methyl Salicylate 29% .......................................................Topical Analgesic

Menthol 7.6% ....................................................................Topical Analgesic

Uses

temporarily relieves the minor pains associated with:

- arthritis
- cramps
- bruises
- sprains
- backache

Warnings

For external use only

When using this product

- use only as directed
- avoid contact with eyes or mucous membranes
- do not bandage tightly or use with a heating pad
- do not apply to wounds or damaged skin

Stop use and ask a doctor if

- condition worsens
- redness is present
- irritation develops
- symptoms persist for more than 7 days or clear up and occur again within a few days

If pregnant or breast-feeding,

ask a health professional before use.

Keep out of reach of children.

If swallowed, get medical help or contact a Poison Control Center right away.

Directions adults and children over 12 years:

- apply generously to affected area
- massage into painful area until thoroughly absorbed into skin
- repeat as necessary, but no more than 4 times daily

children under 12 years: ask a doctor

Inactive ingredients

purified water/aqua/eau, sd alcohol 40-b,

propylene glycol, isopropyl myristate,

glycerin, triethanolamine, carbomer

Allergy alert:

If prone to allergic reaction from aspirin or salicylates, consult a doctor before use.

PACKAGE LABEL

Placeholder Text